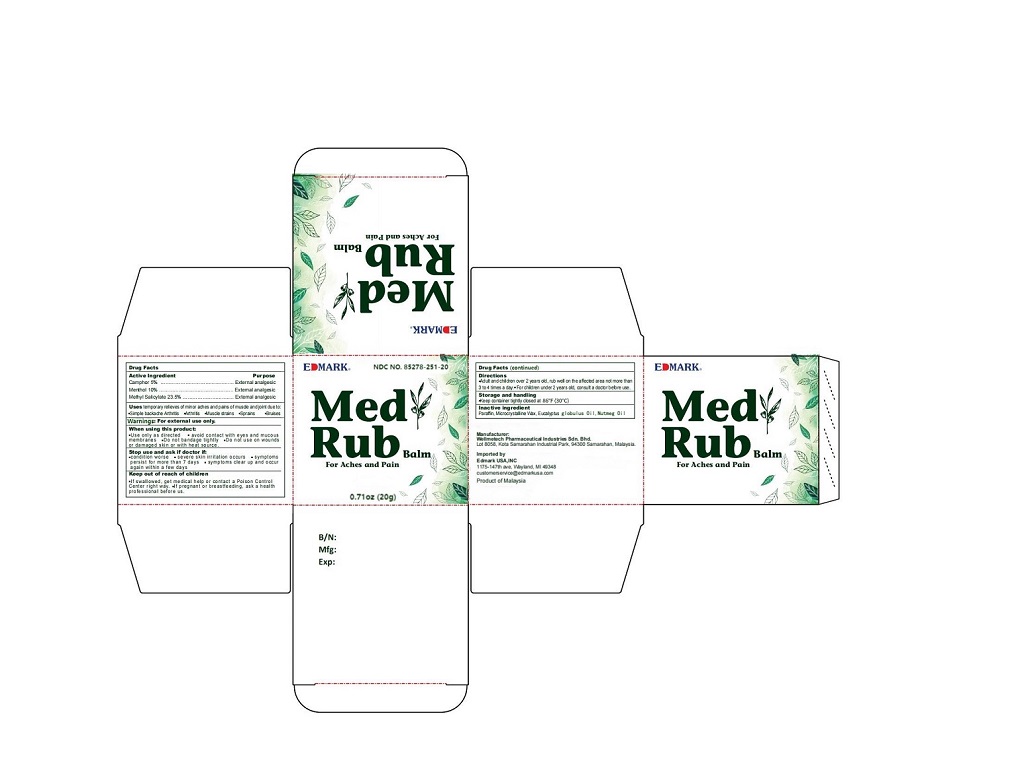 DRUG LABEL: Med Rub Balm
NDC: 85278-251 | Form: OINTMENT
Manufacturer: Wellmetech Pharmaceutical Industries SDN BHD
Category: otc | Type: HUMAN OTC DRUG LABEL
Date: 20251227

ACTIVE INGREDIENTS: CAMPHOR (NATURAL) 5 g/100 g; MENTHOL 10 g/100 g; METHYL SALICYLATE 23.5 g/100 g
INACTIVE INGREDIENTS: PARAFFIN; MICROCRYSTALLINE WAX; EUCALYPTUS GLOBULUS OIL; NUTMEG OIL

Wellmetech Pharmaceutical Industries SDN BHD

Active Ingredient

Camphor 5%

Menthol 10%

Methyl Salicylate 23.5%

Purpose

Menthol External Analgesic
Camphor External Analgesic
Methyl Salicylate External Analgesic

Uses

Temporary relief of minor aches and pains of muscle and joint due to:

- Simple backache arthritis
- Arthritis
- Muscle strains
- Sprains
- Bruises

Warnings

For external use only.

When using this product

- Use only as directed.
- Avoid contact with eyes and mucous membranes.
- Do not bandage tightly.
- Do not use on wounds or damaged skin or with heat source.

Stop use and ask a doctor if

- Condition worse.
- Severe skin irritation occurs.
- Symptoms persist for more than 7 days.
- Symptoms clear up and occur again within a few days.

Keep out of reach of children

- If swallowed, get medical help or contact a Poison Control Center right away.
- If pregnant or breastfeeding, ask a health professional before use.

Directions

- Adult and chldren over 2 years old, rub well on the affected area not more than 3-4 times a day.
- For children under 2 years old, consult a doctor before use.

Storage and handling

Keep container tightly closed at 30°C (86°F).

Inactive ingredient

Paraffin, Microcrystalline Wax, Eucalyptus Globulus Oil, Nutmeg Oil

Manufacturer:

Wellmetech Pharmaceutical Industries Sdn. Bhd.
Lot 8058, Kota Samarahan Industrial Park, 94300 Samarahan, Malaysia

Imported by

Edmark USA, INC
1175-147th Ave, Wayland, MI 49348
customerservice@edmarkusa.com

Product of Malaysia